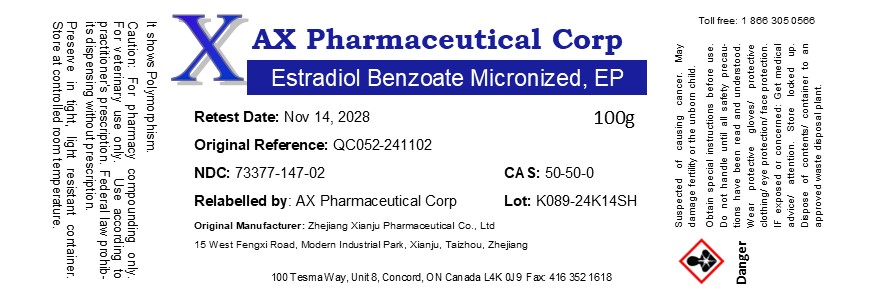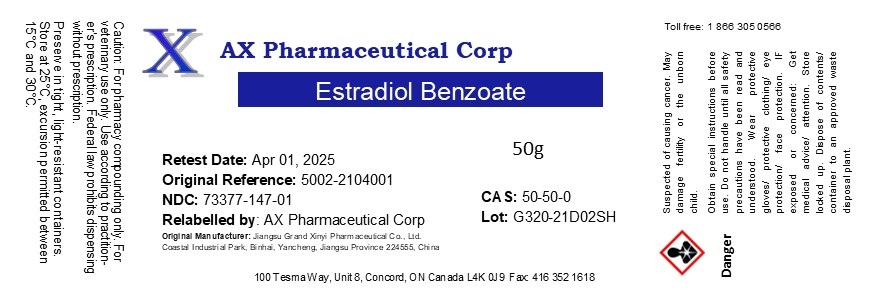 DRUG LABEL: Estradiol Benzoate
NDC: 73377-147 | Form: POWDER
Manufacturer: AX Pharmaceutical Corp
Category: other | Type: BULK INGREDIENT - ANIMAL DRUG
Date: 20250715

ACTIVE INGREDIENTS: ESTRADIOL BENZOATE 1 g/1 g

Estradiol Benzoate